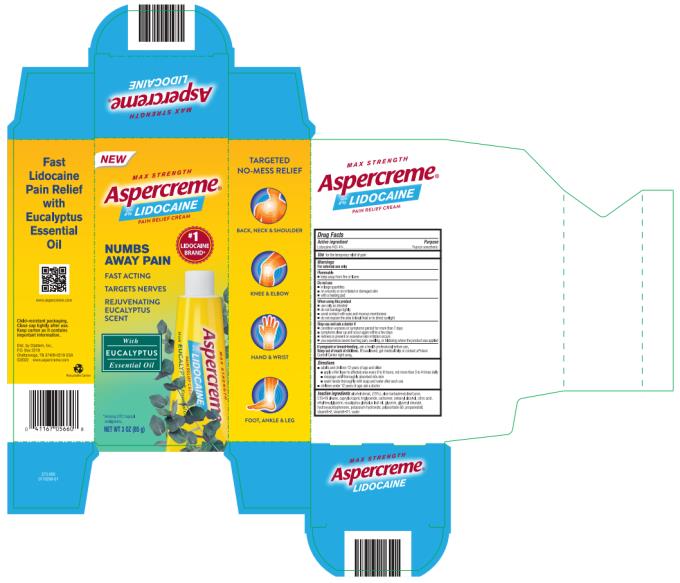 DRUG LABEL: Aspercreme Lidocaine with Eucalyptus Essential Oil
NDC: 41167-0566 | Form: CREAM
Manufacturer: Chattem, Inc.
Category: otc | Type: HUMAN OTC DRUG LABEL
Date: 20231024

ACTIVE INGREDIENTS: LIDOCAINE HYDROCHLORIDE 4 g/100 g
INACTIVE INGREDIENTS: ALOE VERA LEAF; C15-19 ALKANE; MEDIUM-CHAIN TRIGLYCERIDES; CARBOXYPOLYMETHYLENE; CETOSTEARYL ALCOHOL; CITRIC ACID MONOHYDRATE; ETHYLHEXYLGLYCERIN; EUCALYPTUS OIL; GLYCERIN; GLYCERYL MONOSTEARATE; HYDROXYACETOPHENONE; POTASSIUM HYDROXIDE; POLYSORBATE 60; PROPANEDIOL; STEARETH-2; STEARETH-21; WATER; ALCOHOL

Aspercreme Lidocaine with Eucalyptus Essential Oil

Aspercreme Lidocaine with Eucalyptus Essential Oil

Drug Facts

Active ingredient

Lidocaine HCl 4%

Purpose

Topical anesthetic

Use

for the temporary relief of pain

Warnings

For external use only

Flammable: keep away from fire or flame.

Do not use

■ in large quantities

■ on wounds or on irritated or damaged skin

■ with a heating pad

When using this product

■ use only as directed

■ do not bandage tightly

■ avoid contact with eyes and mucous membranes

■ do not expose the area to local heat or to direct sunlight

Stop use and ask a doctor if

■ condition worsens or symptoms persist for more than 7 days

■ symptoms clear up and occur again within a few days

■ redness is present or excessive skin irritation occurs

■ you experience severe burning pain, swelling, or blistering where the product was applied

If pregnant or breast-feeding,

ask a health professional before use.

Keep out of reach of children.

If swallowed, get medical help or contact a Poison Control Center right away.

Directions

■ adults and children 12 years of age and older:

■ apply a thin layer to affected area every 6 to 8 hours, not more than 3 to 4 times daily

■ massage until thoroughly absorbed into skin

■ wash hands thoroughly with soap and water after each use

■ children under 12 years of age: ask a doctor

Inactive ingredients

alcohol denat. (15%), aloe barbadensis leaf juice, C15-19 alkane, caprylic/capric triglyceride, carbomer, cetearyl alcohol, citric acid, ethylhexylglycerin, eucalyptus globulus leaf oil, glycerin, glyceryl stearate, hydroxyacetophenone, potassium hydroxide, polysorbate 60, propanediol, steareth-2, steareth-21, water

373-005

Child-resistant packaging. Close cap tightly after use.

Keep carton as it contains important information.

PRINCIPAL DISPLAY PANEL

Aspercreme
Lidocaine with Eucalyptus Essential Oil
Numbs away pain
NET WT 3 oz (85 g)